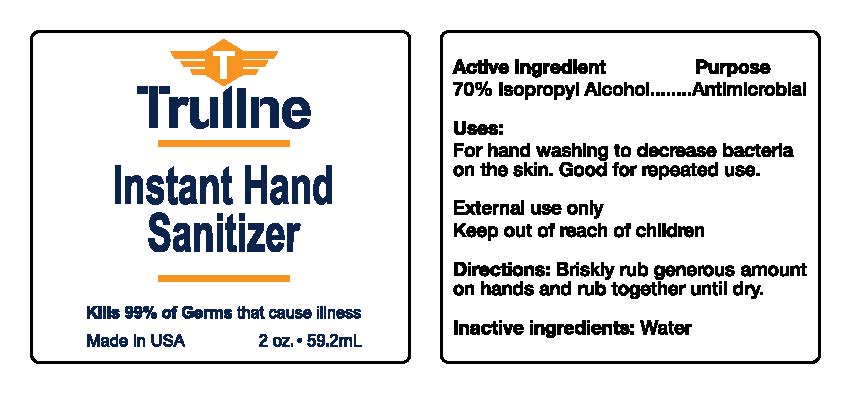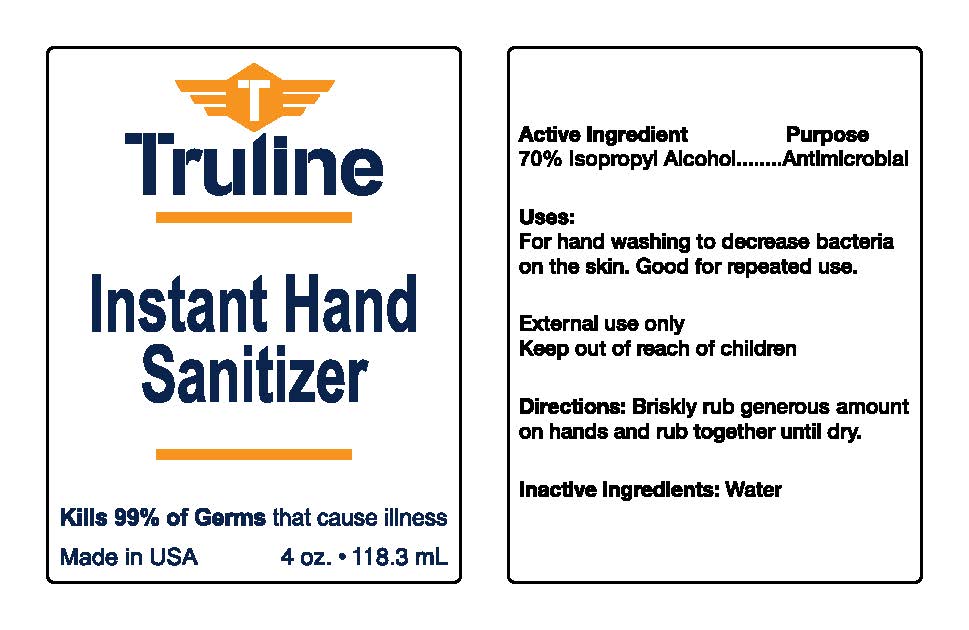 DRUG LABEL: Hand Sanitizer
NDC: 80428-109 | Form: LIQUID
Manufacturer: RACK Furniture Group for Children, LLC.
Category: otc | Type: HUMAN OTC DRUG LABEL
Date: 20200330

ACTIVE INGREDIENTS: ISOPROPYL ALCOHOL 70 1/100 1
INACTIVE INGREDIENTS: WATER 30 1/100 1

This is a hand sanitizer manufactured according to the Temporary Policy for Preparation of Certain Alcohol-Based Hand Sanitizer Products During the Public Health Emergency (CoViD-19); Guidance for Industry.

The hand sanitizer is manufactured using only the following United States Pharmacopoeia (USP) grade ingredients in the preparation of the product (percentage in final product formulation) consistent with World Health Organization (WHO) recommendations:

1. Isopropyl Alcohol (75%, v/v) in an aqueous solution denatured according to Alcohol and Tobacco Tax and Trade Bureau regulations in 27 CFR part 20.
2. Glycerol (1.45% v/v).
3. Hydrogen peroxide (0.125% v/v).
4. Sterile distilled water or boiled cold water.

The firm does not add other active or inactive ingredients. Different or additional ingredients may impact the quality and potency of the product.

Active Ingredient(s)

Isopropyl Alcohol 70% v/v. Purpose: Antimicrobial

Purpose

Antimicrobial, Hand Sanitizer

Use

For hand washing to decrease bacteria on the skin. Good for repeated use.

Warnings

External use only. Keep out of reach of children. Flammable.

Keep out of reach of children.

Directions

- Briskly rub generous amount on hands and rub together until dry.

Inactive ingredients

Water, distilled

Package Label - Principal Display Panel

59.2mL NDC: 80428-109-01

118.3mL NDC: 80428-209-02